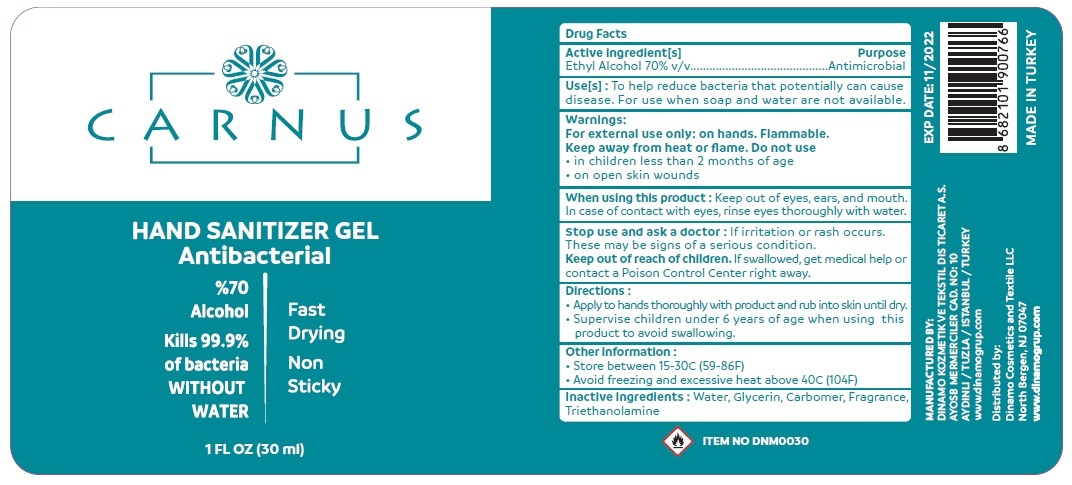 DRUG LABEL: CARNUS HAND SANITIZER - Antibacterial
NDC: 79853-104 | Form: GEL
Manufacturer: DINAMO KOZMETIK VE TEKSTIL DIS TICARET ANONIM SIRKETI
Category: otc | Type: HUMAN OTC DRUG LABEL
Date: 20201202

ACTIVE INGREDIENTS: ALCOHOL 70 mL/100 mL
INACTIVE INGREDIENTS: WATER; GLYCERIN; CARBOMER HOMOPOLYMER, UNSPECIFIED TYPE; TROLAMINE

CARNUS HAND SANITIZER GEL - Antibacterial

Active ingredient[s]

Ethyl Alcohol 70% v/v

Purpose

Antimicrobial

Use[s]:

To help reduce bacteria that potentially can cause disease. For use when soap and water are not available.

Warnings:

For external use only: on hands. Flammable.

Keep away from heat or flame. Do not use

• in children less than 2 months of age

• on open skin wounds

When using this product : Keep out of eyes, ears, and mouth. In case of contact with eyes, rinse eyes thoroughly with water.

Stop use and ask a doctor : If irritation or rash occurs. These may be signs of a serious condition.

Keep out of reach of children. If swallowed, get medical help or contact a Poison Control Center right away.

Directions :

• Apply to hands thoroughly with product and rub into skin until dry.

• Supervise children under 6 years of age when using this product to avoid swallowing.

Other information :

• Store between 15-30C (59-86F)

• Avoid freezing and excessive heat above 40C (104F)

Inactive ingredients :

Water, Glycerin, Carbomer, Fragrance, Triethanolamine

% 70 Alcohol

Kills 99.9% of bacteria WITHOUT WATER

Fast Drying

Non Sticky

MANUFACTURED BY:

DINAMO KOZMETIK VE TEKSTIL DIS TICARET A. S.

AYOSB MERMERCILER CAD. NO:10

AYDINLI / TUZLA / ISTANBUL / TURKEY

www.dinamogrup.com

Distributed by:

Dinamo Cosmetics and Textile LLC

North Bergen, NJ 07047

www.dinamogrup.com

MADE IN TURKEY